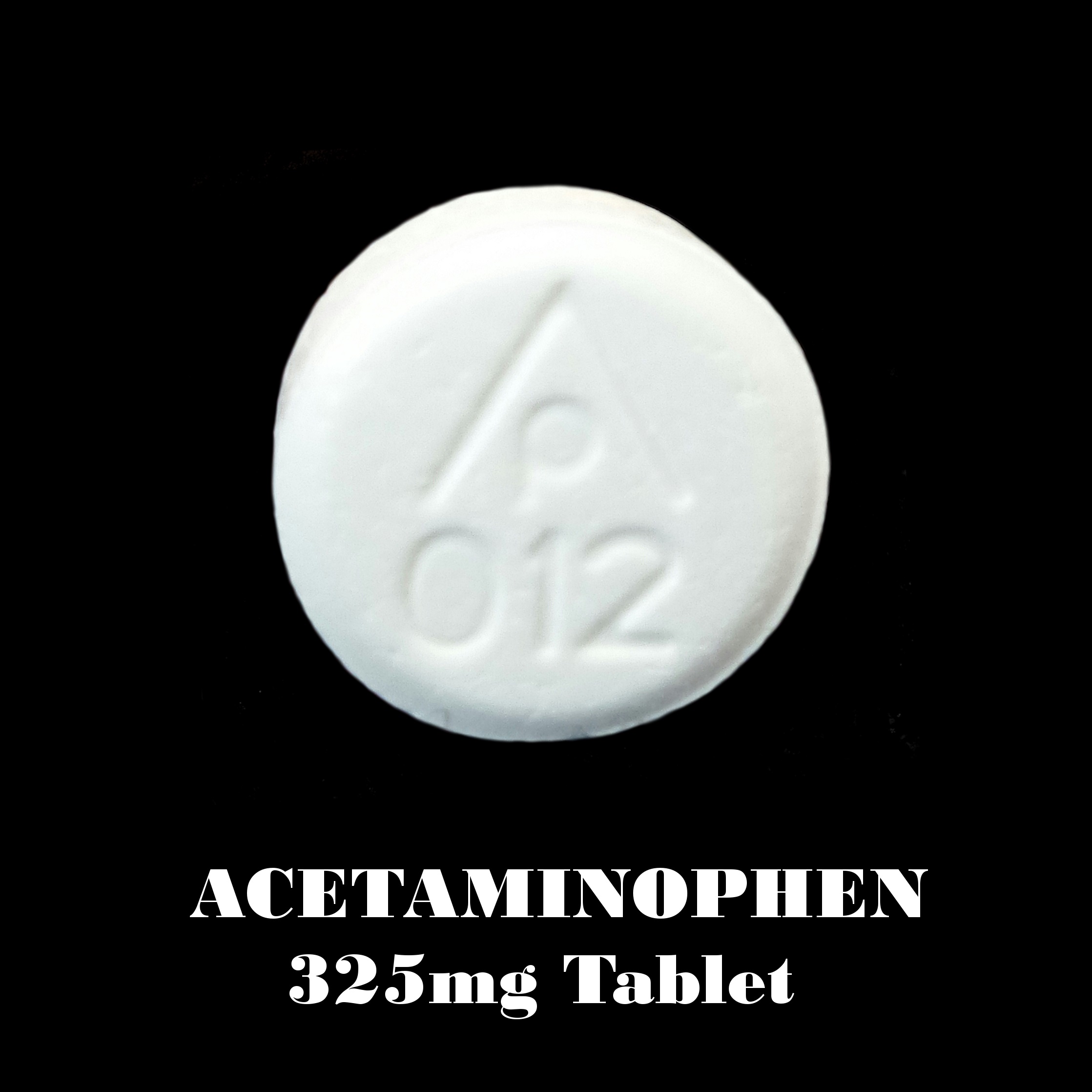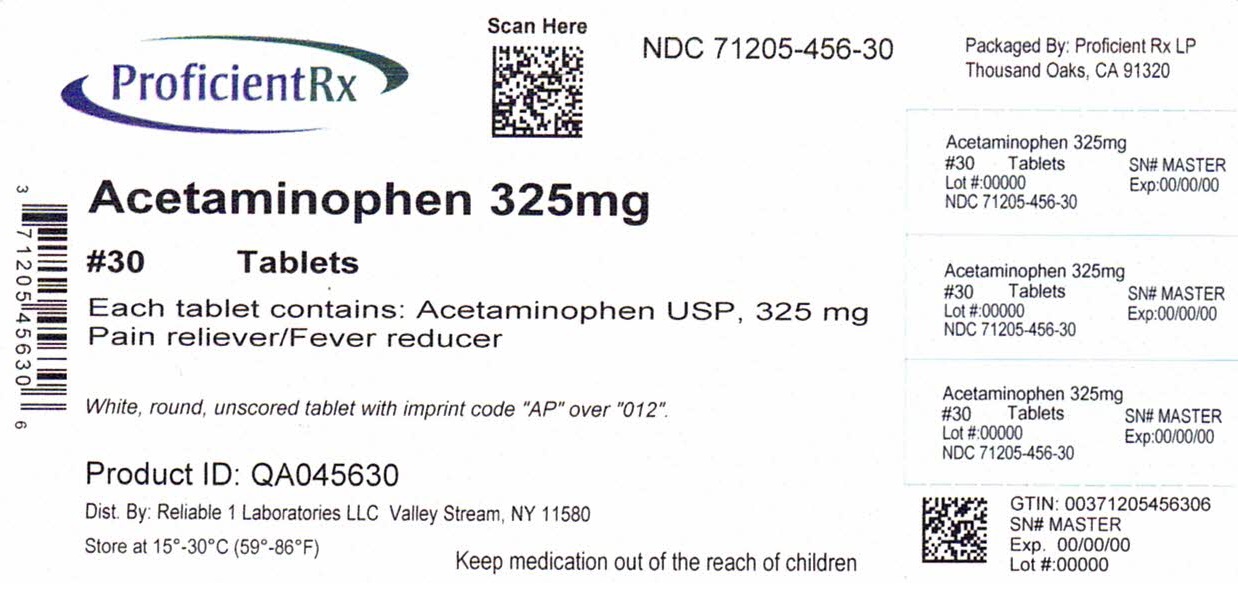 DRUG LABEL: ACETAMINOPHEN 325 MG
NDC: 71205-456 | Form: TABLET
Manufacturer: Proficient Rx LP
Category: otc | Type: HUMAN OTC DRUG LABEL
Date: 20251001

ACTIVE INGREDIENTS: ACETAMINOPHEN 325 mg/1 1
INACTIVE INGREDIENTS: STARCH, CORN; SODIUM STARCH GLYCOLATE TYPE A POTATO; STEARIC ACID; POVIDONE, UNSPECIFIED

Acetaminophen USP 325 mg Tablets

Drug Facts

Active ingredient (in each tablet)

Acetaminophen USP, 325 mg

Purpose

Pain reliever/fever reducer

Uses

- temporarily relieves minor aches and pains due to:
- headache
- muscular aches
- backache
- minor pain of arthritis
- the common cold
- toothache
- premenstrual or menstrual cramps
- temporarily reduces fever

Warnings

Liver warning: This product contains acetaminophen. Severe liver damage may occur if

- adult takes more than 4,000 mg in 24 hours, which is the maximum daily amount
- child takes more than 5 tablets in 24 hours, which is the maximum daily amount
- taken with other drugs containing acetaminophen
- adult has 3 or more alcoholic drinks while using this product

Allergy alert: acetaminophen may cause severe skin reactions. Symptoms may include:

- skin reddening
- blisters
- rash

If a skin reaction occurs, stop use and seek medical help right away.

Do not use with any other drug containing acetaminophen (prescription or nonprescription). If you are not sure whether a drug contains acetaminophen, ask a doctor or pharmacist.

Ask a doctor before use if the user has liver disease

Ask a doctor or pharmacist before use if the user is taking the blood thinning drug warfarin

Stop use and ask a doctor if

- pain gets worse or lasts more than 10 days in adults
- pain gets worse or lasts more than 5 days in children
- fever gets worse or lasts more than 3 days
- new symptoms occur
- redness or swelling is present

These could be signs of a serious condition.

PREGNANCY OR BREAST FEEDING

If pregnant or breast-feeding, ask a health professional before use.

Keep out of reach of children.

Overdose warning: Taking more than the recommended dose (overdose) may cause liver damage. In case of overdose, get medical help or contact a Poison Control Center right away. Quick medical attention is critical for adults as well as for children even if you do not notice any signs or symptoms.

Directions

- do not take more than directed (see overdose warning)

adults and children 12 years and over | take 2 tablets every 4-6 hours while symptoms last, not more than 12 tablets in 24 hours
children 6 to 11 years | take 1 tablet every 4-6 hours while symptoms last, not more than 5 tablets in 24 hours
children under 6 years | do not use

Other information

- store at 15° to 30°C (59° to 86°F)

Inactive ingredients

povidone, pregelatinized corn starch, sodium starch glycolate, stearic acid

Questions or comments?

call 516-341-0666, 8:30 am - 4:30 pm ET, Monday - Friday

TAMPER EVIDENT: DO NOT USE IF IMPRINTED SAFETY SEAL UNDER CAP IS BROKEN OR MISSING

*Reliable 1 Laboratories LLC is not affiliated with the owner of the trademark Tylenol®.

Distributed by: Reliable 1 Laboratories LLC, Valley Stream, NY 11580

Relabeled by: Proficient Rx LP Thousand Oaks, CA 91320

www.reliable1labs.com

PACKAGE LABEL

NDC 71205-456-30

Regular Strength

Acetaminophen USP 325 mg

PAIN RELIEVER

FEVER REDUCER

30 TABLETS

*Compare to Active Ingredient in Regular Strength TYLENOL®